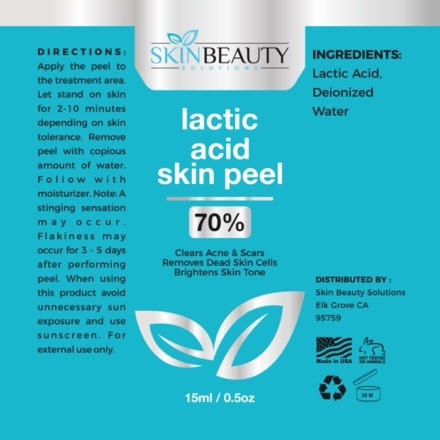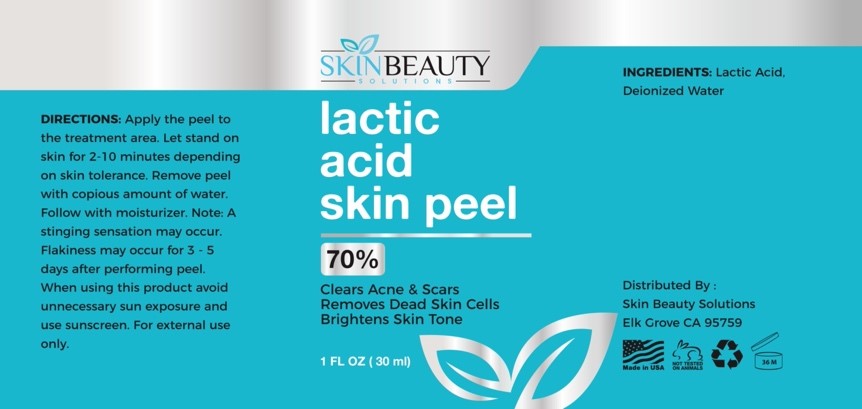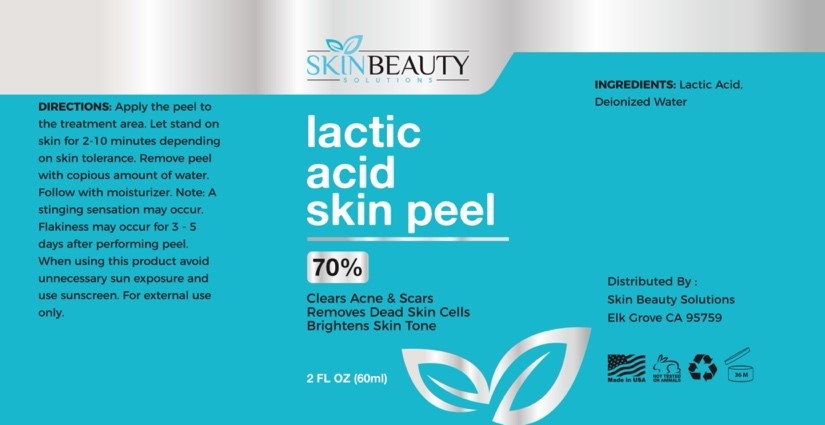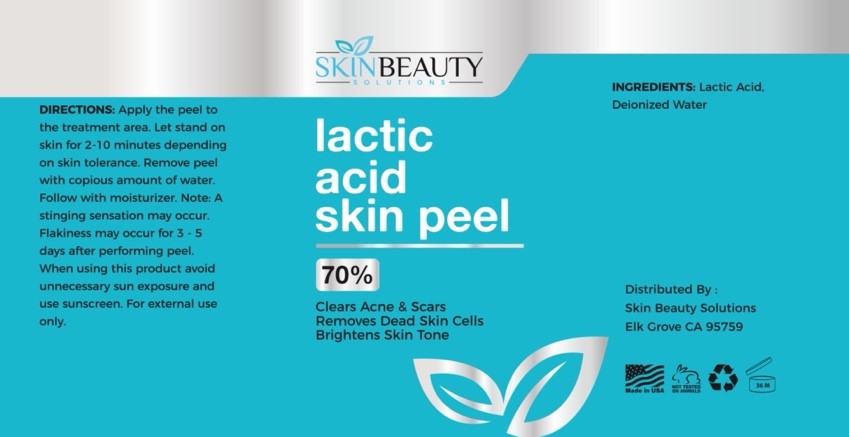 DRUG LABEL: LACTIC Acid 70 Skin Chemical Peel
NDC: 84785-0022 | Form: SOLUTION
Manufacturer: Gazebo Wellness SKIN LLC
Category: otc | Type: HUMAN OTC DRUG LABEL
Date: 20241216

ACTIVE INGREDIENTS: LACTIC ACID 0.3 mg/30 mL
INACTIVE INGREDIENTS: WATER

DOSAGE AND ADMINISTRATION

Apply the peel to the treatment area. Let stand on skin for 2-10 minutes depending on skin tolerance. Remove peel with copious amount of water. Follow with moisturizer. Note: A stinging sensation may occur. Flakiness may occur for 3-5 days after performing peel. When using this product avoid unnecessary sun exposure and use sunscreen. For external use only.

WARNINGS

DIRECTIONS: Apply the peel to the treatment area. Let stand on skin for 2-10 minutes depending on skin tolerance. Remove peel with copious amount of water. Follow with moisturizer. Note: A stinging sensation may occur. Flakiness may occur for 3-5 days after performing peel. When using this product avoid unnecessary sun exposure and use sunscreen. For external use only.

Inactive ingredient: Deionized Water.

Active ingredient: Lactic Acid.

INDICATIONS AND USAGE

DIRECTIONS: Apply the peel to the treatment area. Let stand on skin for 2-10 minutes depending on skin tolerance. Remove peel with copious amount of water. Follow with moisturizer. Note: A stinging sensation may occur. Flakiness may occur for 3-5 days after performing peel. When using this product avoid unnecessary sun exposure and use sunscreen. For external use only.

keep out of reach of children

PURPOSE

lactic
acid skin peel
50%
Clears Acne & Scars Removes Dead Skin Cells Brightens Skin Tone

Distributed By:
Skin Beauty Solutions Elk Grove CA 95759

PACKAGE LABEL

Content of labeling